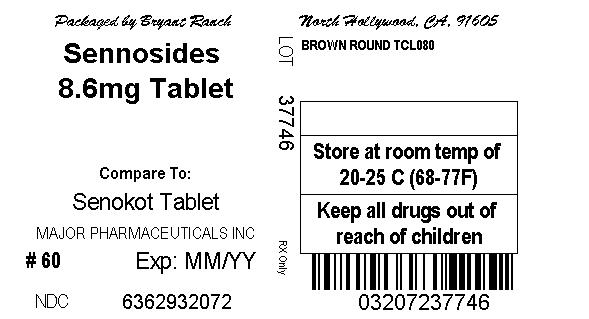 DRUG LABEL: Senna-Lax
NDC: 63629-3207 | Form: TABLET, FILM COATED
Manufacturer: Bryant Ranch Prepack
Category: prescription | Type: HUMAN PRESCRIPTION DRUG LABEL
Date: 20121012

ACTIVE INGREDIENTS: SENNOSIDES A AND B 8.6 mg/1 1
INACTIVE INGREDIENTS: ACACIA; CALCIUM CARBONATE; CROSCARMELLOSE SODIUM; DEXTROSE; HYPROMELLOSES; MAGNESIUM STEARATE; MALTODEXTRIN; CELLULOSE, MICROCRYSTALLINE; PROPYLENE GLYCOL; SILICON DIOXIDE; STEARIC ACID; TRIACETIN

Sennosides 8.6 mg

Active ingredient (in each tablet)

Sennosides 8.6 mg

Purpose

Laxative

Uses

- relieves occasional constipation (irregularity)
- generally produces a bowel movement in 6-12 hours

Warnings

Do not use

- laxative products for longer than 1 week unless directed by a doctor

Ask a doctor before use if you have

- stomach pain
- nausea
- vomiting
- noticed a sudden change in bowel habits that continues over a period of 2 weeks

Stop use and ask a doctor if

you have rectal bleeding or fail to have a bowel movement after use of a laxative.

These may indicate a serious condition.

If pregnant or breast-feeding,

ask a health professional before use.

Keep out of reach of children.

In case of overdose, get medical help or contact a Poison Control Center right away.

Directions

- take preferably at bedtime or as directed by a doctor

age | starting dosage | maximum dosage
adults and children 12 years of age and older | 2 tablets once a day | 4 tablets twice a day
children 6 to under 12 years of age | 1 tablet once a day | 2 tablets twice a day
children 2 to under 6 years of age | 1/2 tablet once a day | 1 tablet twice a day
children under 2 years of age | ask a doctor | ask a doctor

Inactive ingredients

Acacia Gum, Calcium Carbonate, Croscarmellose Sodium, Dextrose, Hypromellose, Magnesium Stearate, Maltodextrin, Microcrystalline Cellulose, Propylene Glycol, Silicon Dioxide, Stearic Acid, Triacetin.

Questions?

Adverse Drug Event call (800) 616-2471